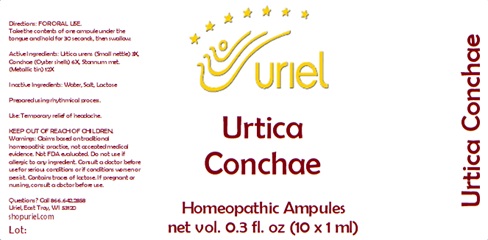 DRUG LABEL: Urtica Conchae
NDC: 48951-9386 | Form: LIQUID
Manufacturer: Uriel Pharmacy Inc.
Category: homeopathic | Type: HUMAN OTC DRUG LABEL
Date: 20241209

ACTIVE INGREDIENTS: URTICA URENS 3 [hp_X]/1 mL; OSTREA EDULIS SHELL 6 [hp_X]/1 mL; TIN 12 [hp_X]/1 mL
INACTIVE INGREDIENTS: WATER; SODIUM CHLORIDE; LACTOSE

Urtica Conchae

INDICATIONS AND USAGE

Directions: FOR ORAL USE.

DOSAGE AND ADMINISTRATION

Take the contents of one ampule under the tongue and hold for 30 seconds, then swallow.

ACTIVE INGREDIENT

Active Ingredients: Urtica urens (Small nettle) 3X, Conchae (Oyster shells) 6X, Stannum met. (Metallic tin) 12X

Inactive Ingredients: Water, Salt, Lactose

Prepared using rhythmical processes.

PURPOSE

Use: Temporary relief of headache.

KEEP OUT OF REACH OF CHILDREN.

WARNINGS

Warnings: Claims based on traditional homeopathic practice, not accepted medical evidence. Not FDA evaluated. Do not use if allergic to any ingredient. Contains traces of lactose. Consult a doctor before use for serious conditions or if conditions worsen or persist. If pregnant or nursing, consult a doctor before use.

QUESTIONS

Questions? Call 866.642.2858 Made by Uriel, East Troy, WI 53120 shopuriel.com Lot: